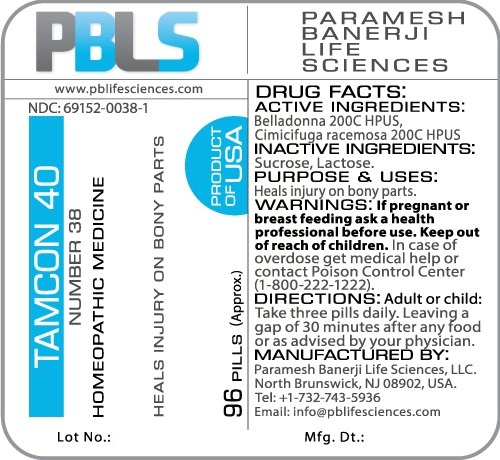 DRUG LABEL: Tamcon 40 (Number 38)
NDC: 69152-0038 | Form: PELLET
Manufacturer: Paramesh Banerji Life Sciences LLC
Category: homeopathic | Type: HUMAN OTC DRUG LABEL
Date: 20161111

ACTIVE INGREDIENTS: ATROPA BELLADONNA 200 [hp_C]/1 1; BLACK COHOSH 200 [hp_C]/1 1
INACTIVE INGREDIENTS: LACTOSE; SUCROSE

DRUG FACTS: Active Ingredients

Belladonna 200C HPUS, Cimicifuga racemosa 200C HPUS

Inactive Ingredients

Sucrose, Lactose

Purpose

Heals injury on bony parts

Uses

Heals injury on bony parts

Warnings

If pregnant or breast feeding ask a health professional before use.

Keep out of reach of children. In case of overdose, get medical help or contact a Poison Control Center (1-800-222-1222) right away.

Direction

Adult or child: Take three pills daily. Leaving a gap of 30 minutes after any food or as advised by your physician.

Manufactured by

Paramesh Banerji Life Sciences, LLC.

North Brunswick, NJ 08902, USA.

Tel: +1-732-743-5936

Email: info@pblifesciences.com

Principal Display Panel

NDC: 69152-0038-1

Tamcon 40

Number 38

Homeopathic Medicine

Heals injury on bony parts

96 Pills (Approx.)

Product of USA